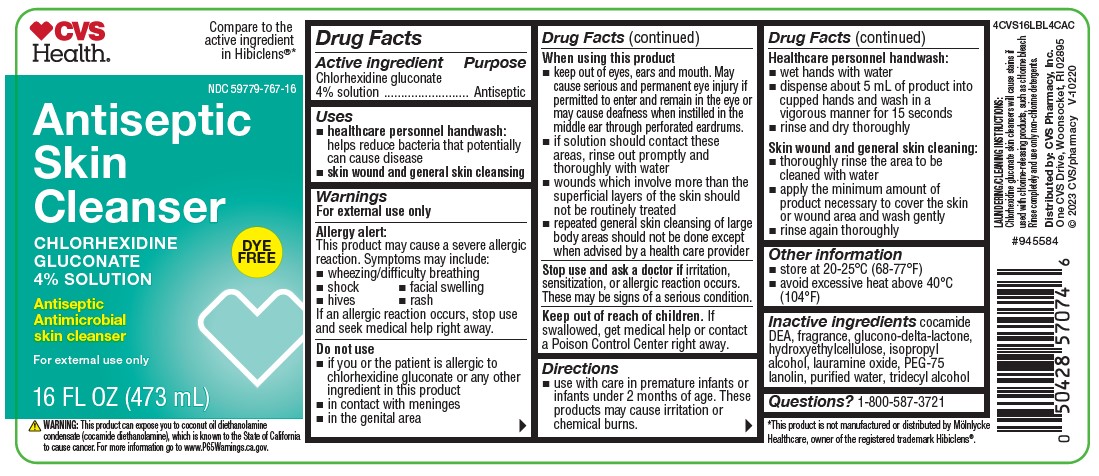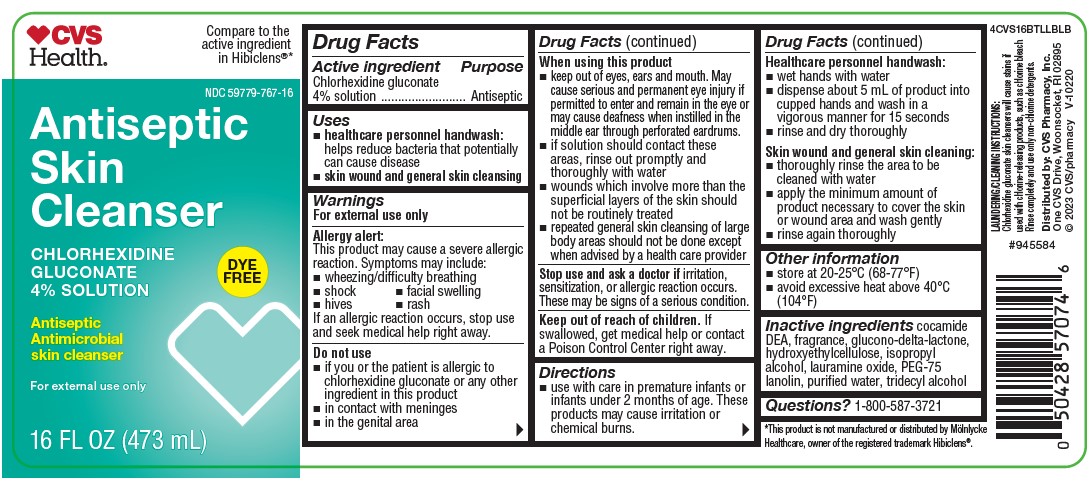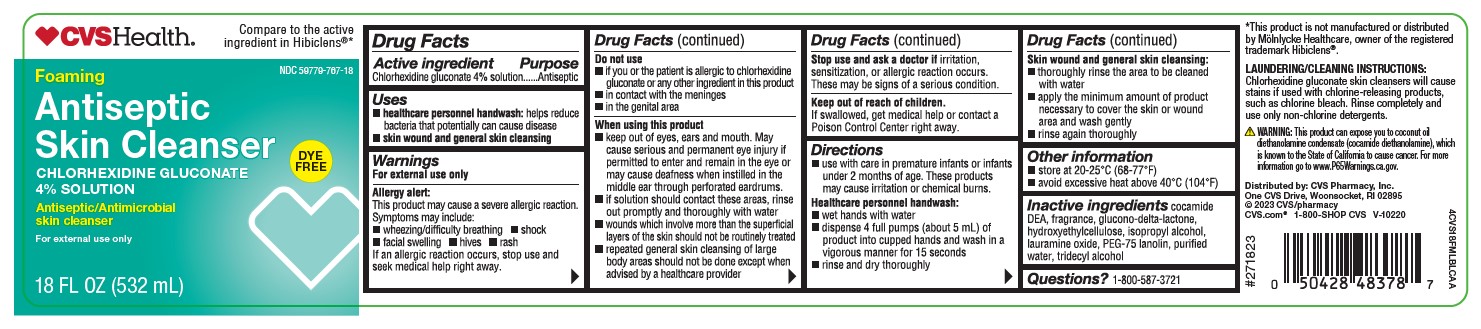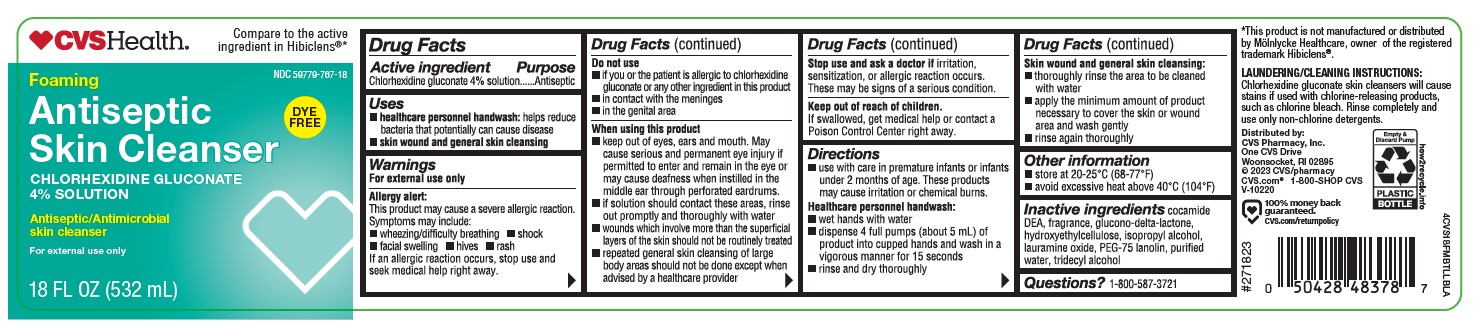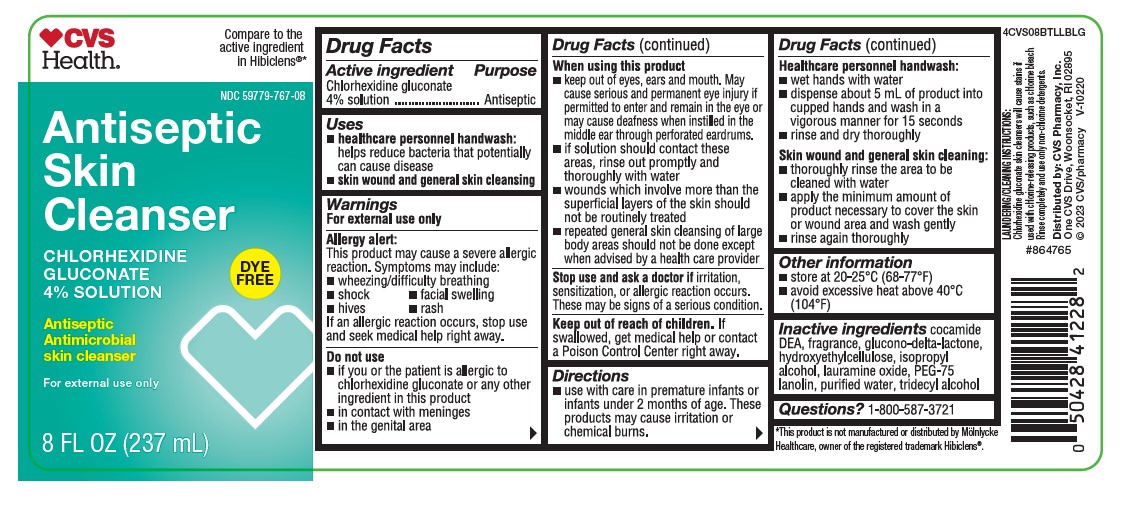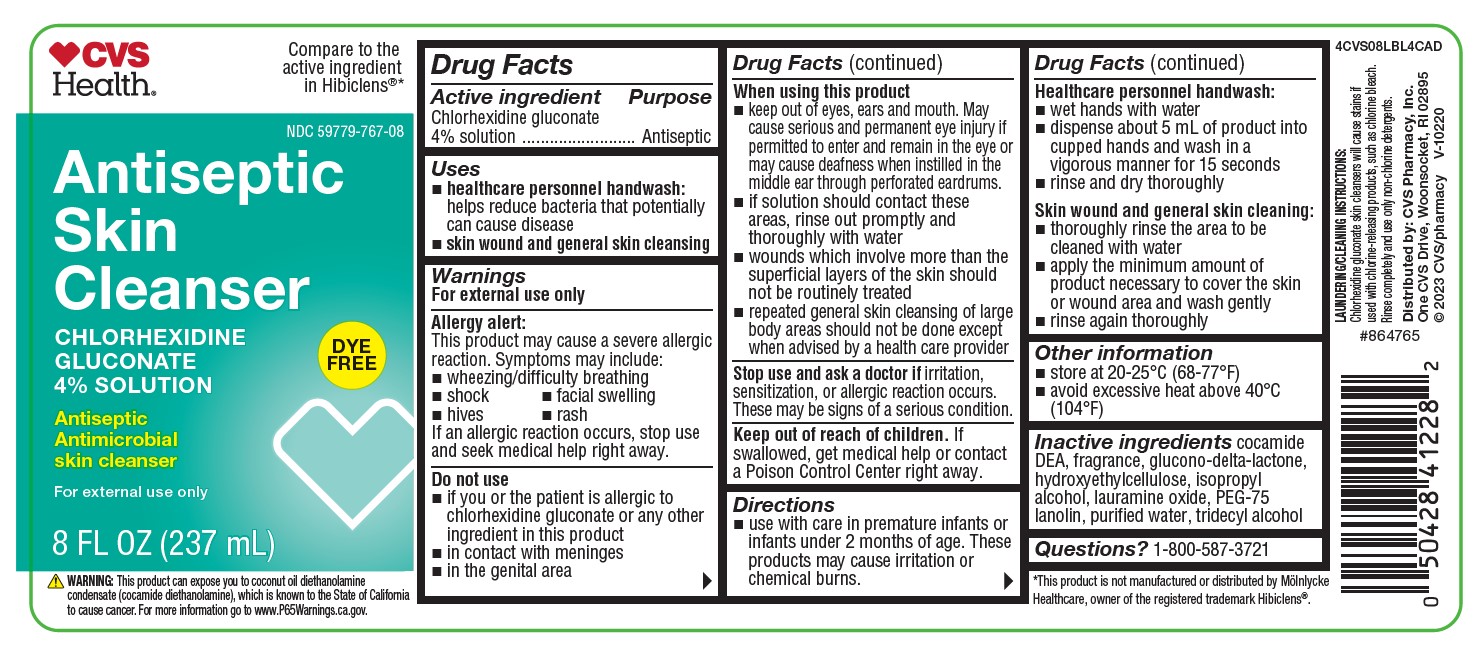 DRUG LABEL: Antiseptic Skin Cleanser
NDC: 0116-0767 | Form: LIQUID
Manufacturer: Xttrium Laboratories, Inc.
Category: otc | Type: HUMAN OTC DRUG LABEL
Date: 20251208

ACTIVE INGREDIENTS: CHLORHEXIDINE GLUCONATE 4 g/100 mL
INACTIVE INGREDIENTS: GLUCONOLACTONE; PEG-75 LANOLIN; TRIDECYL ALCOHOL; COCO DIETHANOLAMIDE; HYDROXYETHYL CELLULOSE (2000 CPS AT 1%); ISOPROPYL ALCOHOL; LAURAMINE OXIDE; WATER

XTT CVS 4% CHG 8oz, 8oz CA, 16oz, 16oz CA,
XTT COMP 18oz, 18oz CA

ACTIVE INGREDIENT

Chlorhexidine gluconate 4% Solution

Purpose

Antiseptic

Uses

- healthcare personnel handwash: helps reduce bacteria that potentially can cause disease
- skin wound and general cleansing

Warnings

For external use only

Allergy alert:

This product may cause a severe allergic reaction. Symptoms may include:

- wheezing/difficulty breathing
- shock
- facial swelling
- hives
- rash

If an allergic reaction occurs, stop use and seek medical help right away.

Do not use

- if you or the patient is allergic to chlorhexidine gluconate or any other ingredient in this product
- in contact with meninges
- in the genital area

When using this product

- keep out of eyes, ears, and mouth. May cause serious and permanent eye injury if permitted to enter and remain in the eye or may cause deafness when instilled in the middle ear through perforated eardrums.
- if solution should contact these areas, rinse out promptly and thoroughly with water
- wound which involve more than the superficial layers of the skin should not be routinely treated
- repeated general skin cleansing of large body areas should not be done except when advised by a health care provider

Stop use and ask a doctor

if irritation, sensitization, or allergic reaction occurs. These may be signs of a serious condition.

Keep out of reach of children

If swallowed, get medical help or contact a Poison Control Center right away.

Direction

- use with care in premature infants or infants under 2 months of age. These products may cause irritation or chemical burns.

Healthcare personnel handwash:

- wet hands with water
- dispense about 5 ml of product into cupped hands and wash in a vigorous manner for about 15 seconds
- rinse and dry thoroughly

Skin wound and general skin cleansing:

- thoroughly rinse the area to be cleaned with water
- apply the minimum amount of product necessary to cover the skin or wound area and wash gently
- rinse again thoroughly

other information

- store at 20-25 C (68-77 F)
- avoid excessive heat above 40 C (104 F)

Inactive ingredients

cocamide DEA, fragrance, glucono-delta-lactone, hydroxyethylcellulose, isopropyl alcohol, lauramine oxide, PEG-75 lanolin, purified water, tridecyl alcohol

Questions or comments?

1-800-587-3721

Uses

Doseage and Adminisration

Packaging

CVS Health

Compare to the active ingredient in Hibiclens®

NDC 59779-767-08

Antiseptic Skin Cleanser

CHLORHEXIDINE GLUCONATE 4% SOLUTION

Antiseptic / Antimicrobial skin cleanser

For external use only

TAMPER EVIDENT: DO NOT USE IF SHRINK SEAL NECKBAND IS BROKEN OR MISSING

8 fl oz (237 mL)

4CVS08BTLLBLG

CVS Health

Comapre to the active ingredient in Hibiclens®

NDC 59779-767-08

Antiseptic Skin Cleanser

CHLORHEXIDINE GLUCONATE 4% SOLUTION

Antiseptic / Antimicrobial skin cleanser

For external use only

TAMPER EVIDENT: DO NOT USE IF SHRINK SEAL NECKBAND IS BROKEN OR MISSING

8 fl oz (237 mL)

4CVS08LBL4CAD

CVS Health

Compare to the active ingredient in Hibiclens®

NDC 59779-767-16

Antiseptic Skin Cleanser

CHLORHEXIDINE GLUCONATE 4% SOLUTION

Antiseptic / Antimicrobial skin cleanser

For external use only

TAMPER EVIDENT: DO NOT USE IF SHRINK SEAL NECKBAND IS BROKEN OR MISSING

16 fl oz (473 mL)

4CVS16BTLLBLB

CVS Health

Comapre to the active ingredient in Hibiclens®

NDC 59779-767-16

Antiseptic Skin Cleanser

CHLORHEXIDINE GLUCONATE 4% SOLUTION

Antiseptic / Antimicrobial skin cleanser

For external use only

TAMPER EVIDENT: DO NOT USE IF SHRINK SEAL NECKBAND IS BROKEN OR MISSING

16 fl oz (473 mL)

4CVS16LBL4CAC

CVS Health

Comapre to the active ingredient in Hibiclens®

NDC 59779-767-18

FOAMING

Antiseptic Skin Cleanser

CHLORHEXIDINE GLUCONATE 4% SOLUTION

Antiseptic / Antimicrobial skin cleanser

Clinically proven to reduce bacteria on skin

18 fl oz (532 mL)

For external use only

4CVS18FMBTLLBLA

CVS Health

Compare to the active ingredient in Hibiclens®

NDC 59779-767-18

FOAMING

Antiseptic Skin Cleanser

CHLORHEXIDINE GLUCONATE 4% SOLUTION

Antiseptic / Antimicrobial skin cleanser

Clinically proven to reduce bacteria on skin

18 fl oz (532 mL)

For external use only

4CVS18FMLBLCAA